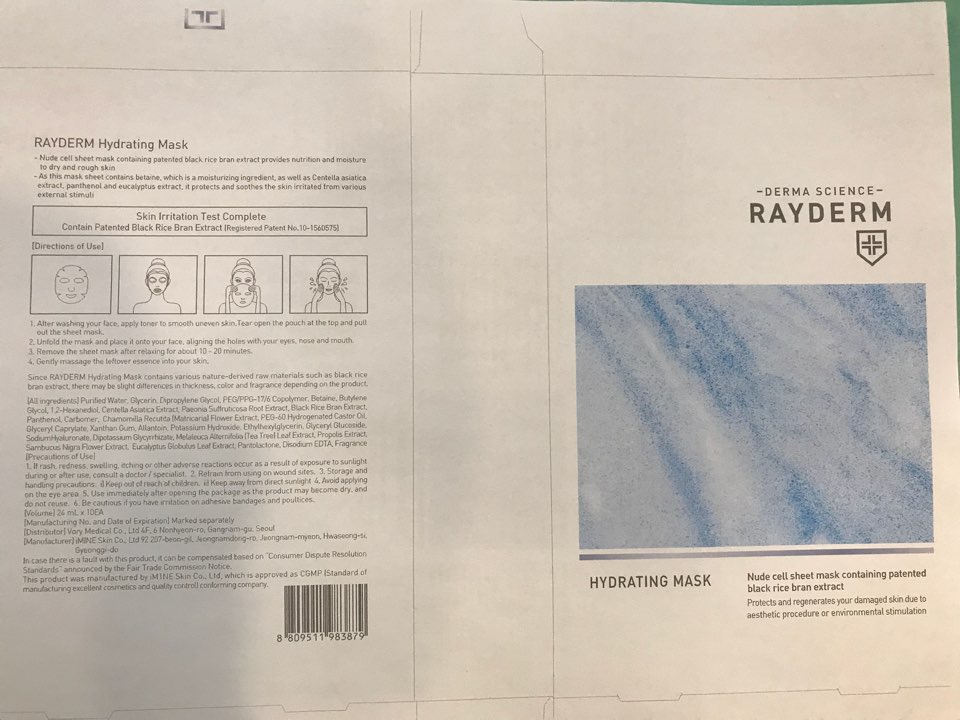 DRUG LABEL: Rayderm Hydrating Mask
NDC: 72543-001 | Form: LIQUID
Manufacturer: VORY MEDICAL. Inc
Category: otc | Type: HUMAN OTC DRUG LABEL
Date: 20181011

ACTIVE INGREDIENTS: glycerin 3.84 g/24 mL; ALLANTOIN 0.12 g/24 mL
INACTIVE INGREDIENTS: water; DIPROPYLENE GLYCOL; PEG/PPG-17/6 COPOLYMER; BETAINE; BUTYLENE GLYCOL; 1,2-HEXANEDIOL; CENTELLA ASIATICA; PAEONIA SUFFRUTICOSA ROOT; PANTHENOL; PEG-60 HYDROGENATED CASTOR OIL; GLYCERYL CAPRYLATE; XANTHAN GUM; POTASSIUM HYDROXIDE; ETHYLHEXYLGLYCERIN; MELALEUCA ALTERNIFOLIA LEAF; SAMBUCUS CANADENSIS FLOWER; EUCALYPTUS GLOBULUS LEAF

ACTIVE INGREDIENT

Glycerin (16%) - Skin Protectact

Allantoin (00.5%) - Skin Protectact

INACTIVE INGREDIENT

Purified Water, Dipropylene Glycol, PEG/PPG-17/6 Copolymer, Betaine, Butylene Glycol, 1,2-Hexanediol, Centella Asiatica Extract, Paeonia Suffruticosa Root Extract, Black Rice Bran Extract, Panthenol, Carbomer, Chamomilla Recutita (Matricaria) Flower Extract, PEG-60 Hydrogenated Castor Oil, Glyceryl Caprylate, Xanthan Gum, Potassium Hydroxide, Ethylhexylglycerin, Glyceryl Glucoside, Sodium Hyaluronate, Dipotassium Glycyrrhizate, Melaleuca Alternifolia (Tea Tree) Leaf Extract, Propolis Extract, Sambucus Nigra Flower Extract, Eucalyptus Globulus Leaf Extract, Pantolactone, Disodium EDTA, Fragrance

PURPOSE

Skin Protectact

WARNINGS

Precautions of Use
1. If rash, redness, swelling, itching or other adverse reactions occur as a result of exposure to sunlight during or after use, consult a doctor / specialist.
2. Refrain from using on wound sites.
3. Storage and handling precautions:
i) Keep out of reach of children.
ii) Keep away from direct sunlight
4. Avoid applying on the eye area
5. Use immediately after opening the package as the product may become dry, and do not reuse.
6. Be cautious if you have irritation on adhesive bandages and poultices.

INDICATIONS & USAGE

1. After washing your face, apply toner to smooth uneven skin.Tear open the pouch at the top and pull out the sheet mask.
2. Unfold the mask and place it onto your face, aligning the holes with your eyes, nose and mouth.
3. Remove the sheet mask after relaxing for about 10 - 20 minutes.
4. Gently massage the leftover essence into your skin.

DOSAGE & ADMINISTRATION

1. After washing your face, apply toner to smooth uneven skin.Tear open the pouch at the top and pull out the sheet mask.
2. Unfold the mask and place it onto your face, aligning the holes with your eyes, nose and mouth.
3. Remove the sheet mask after relaxing for about 10 - 20 minutes.
4. Gently massage the leftover essence into your skin.